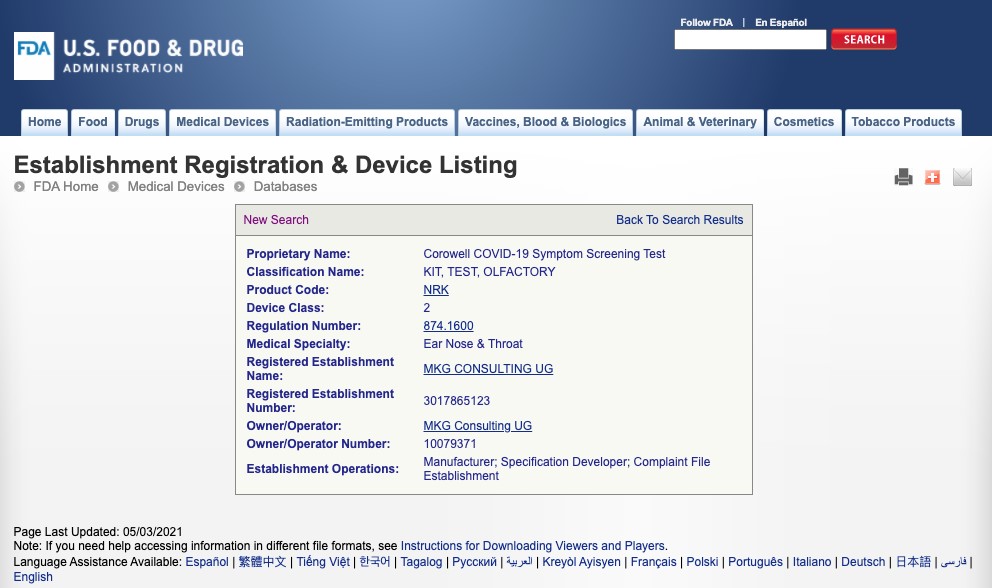 DRUG LABEL: Corowell COVID-19 Symptom Screening Test
NDC: 72678-004
Manufacturer: NATIONAL BIO GREEN SCIENCES LIMITED LIABILITY COMPANY
Category: other | Type: MEDICAL DEVICE
Date: 20210729

COVID Symptom Screen Kit

Product Label

NA